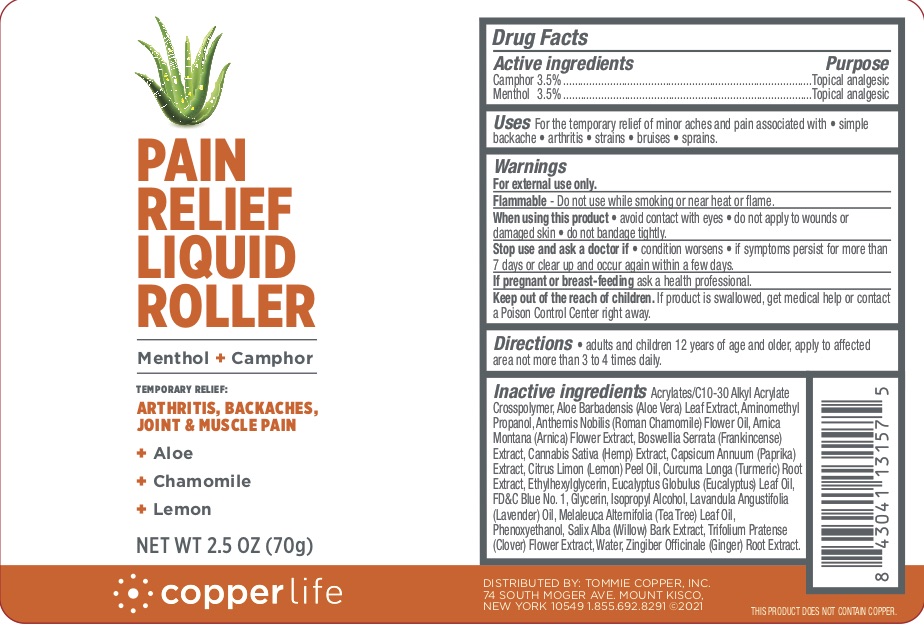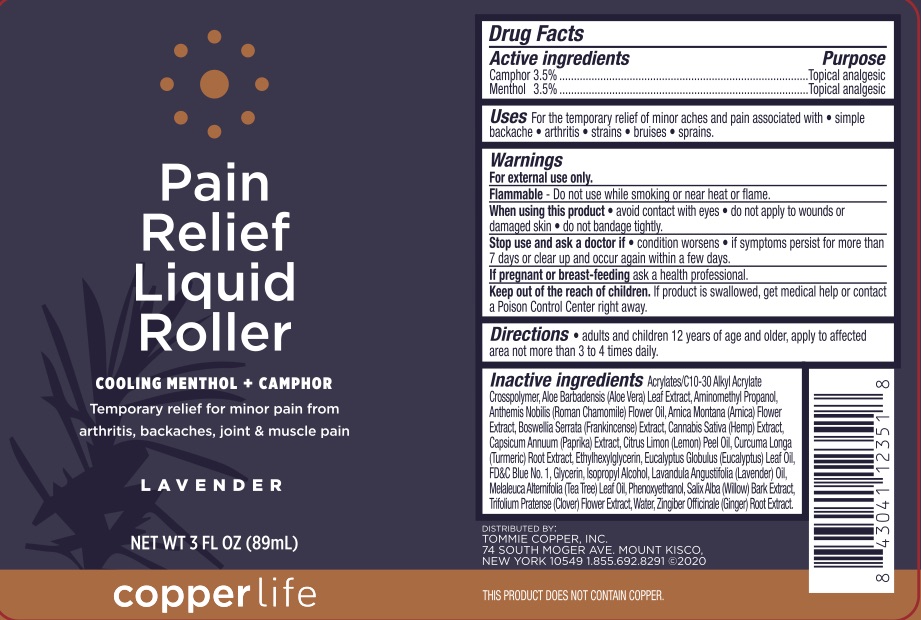 DRUG LABEL: Tommie Copper Pain Relief Roller
NDC: 72562-125 | Form: LIQUID
Manufacturer: Tommie Copper, Inc.
Category: otc | Type: HUMAN OTC DRUG LABEL
Date: 20241215

ACTIVE INGREDIENTS: CAMPHOR (SYNTHETIC) 3.5 g/100 mL; MENTHOL 3.5 g/100 mL
INACTIVE INGREDIENTS: TRIFOLIUM PRATENSE FLOWER; GINGER; SALIX ALBA BARK; ETHYLHEXYLGLYCERIN; PHENOXYETHANOL; CHAMAEMELUM NOBILE FLOWER OIL; WATER; EUCALYPTUS OIL; FD&C BLUE NO. 1; GLYCERIN; ALOE VERA LEAF; ISOPROPYL ALCOHOL; INDIAN FRANKINCENSE; CANNABIS SATIVA SEED; ECHINACEA ANGUSTIFOLIA; ARNICA MONTANA FLOWER; PAPRIKA; CARBOMER INTERPOLYMER TYPE A (ALLYL SUCROSE CROSSLINKED); AMINOMETHYLPROPANOL; LEMON OIL; TURMERIC; TEA TREE OIL; LAVENDER OIL

Pain Relief Liquid Roller

ACTIVE INGREDIENT

Camphor 3.5%, Menthol 3.5%

PURPOSE

Topical Analgesic

INDICATIONS AND USAGE

For the temporary relief of minor aches and pain associated with simple backaches, arthritis, strains, bruises, and sprains.

WARNINGS

For external use only. Flammable--Do not use while smoking or near heat or flame. When using this product avoid contact with eyes, do not apply to wounds or damaged skin, and do not bandage tightly. Stop use and ask a doctor if condition worsens, if symptoms persist for more than 7 days or clear up and occur again within a few days.

PREGNANCY OR BREAST FEEDING

If pregnant or breast-feeding ask a health professional.

KEEP OUT OF REACH OF CHILDREN

If swallowed, get medical help or contact a Poison Control Center right away.

DOSAGE AND ADMINISTRATION

Adults and children 12 years of age and older, apply to the affected area not more than 3 to 4 times daily.

INACTIVE INGREDIENT

Acrylates/C10-30 Alkyl Acrylate Crosspolymer, Aloe Barbadensis (Aloe Vera) Leaf Extract, Aminomethyl Propanol, Anthemis Nobilis (Roman Chamomile) Flower Oil, Arnica Montana (Arnica) Flower Extract, Boswellia Serrata (Frankincense) Extract, Cannabis Sativa (Hemp) Extract, Capsicum Annuum (Paprika) Extract, Citrus Limon (Lemon) Peel Oil, Curcuma Longa (Tumeric) Root Extract, Ethyhexylglycerin, Eucalyptus Globulus (Eucalyptus) Leaf Oil, FD&C Blue No 1, Glycerin, Isopropyl Alcohol, Lavandula Angustifolia (Lavender) Oil, Melaleuca Alternifolia (Tea Tree) Leaf Oil, Phenoxyethanol, Salix Alba (Willow) Bark Extract, Trifolium Pratense (Clover) Flower Extract, Water, Zingiber Officinale (Ginger) Root Extract.